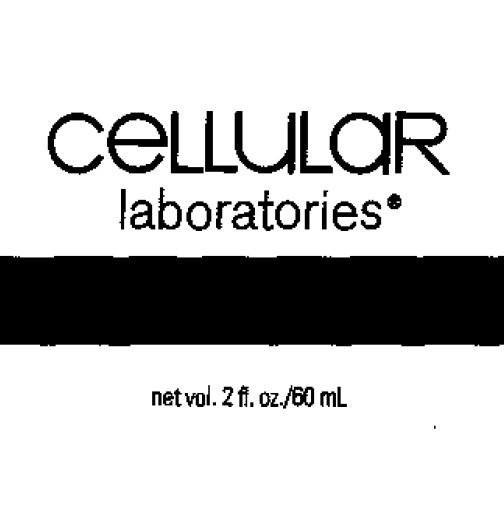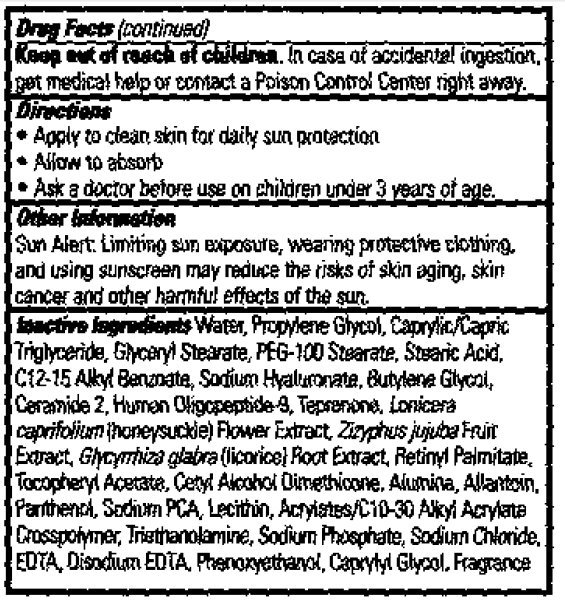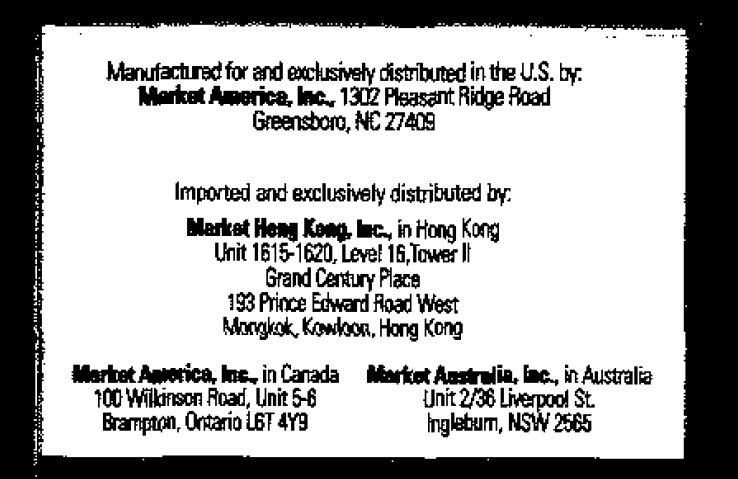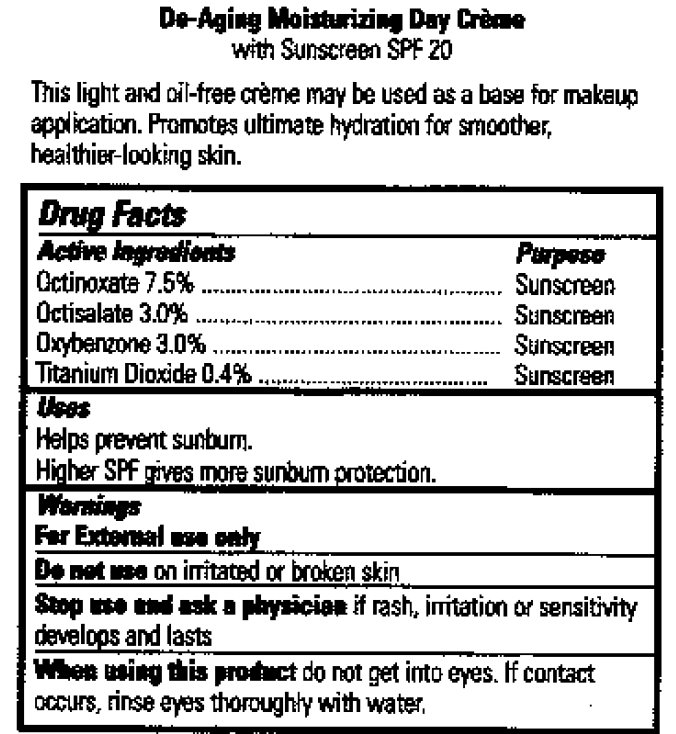 DRUG LABEL: De-Aging Moisturizing Day Creme With Sunscreen SPF 20
NDC: 76209-234 | Form: CREAM
Manufacturer: Market America
Category: otc | Type: HUMAN OTC DRUG LABEL
Date: 20231212

ACTIVE INGREDIENTS: OCTINOXATE 75 mg/1 mL; OCTISALATE 30 mg/1 mL; OXYBENZONE 30 mg/1 mL; TITANIUM DIOXIDE 4 mg/1 mL
INACTIVE INGREDIENTS: WATER; PROPYLENE GLYCOL; MEDIUM-CHAIN TRIGLYCERIDES; GLYCERYL MONOSTEARATE; PEG-100 STEARATE; STEARIC ACID; ALKYL (C12-15) BENZOATE; HYALURONATE SODIUM; BUTYLENE GLYCOL; CERAMIDE 2; JUJUBE FRUIT; VITAMIN A PALMITATE; ALUMINUM OXIDE; PANTHENOL; SODIUM PYRROLIDONE CARBOXYLATE; CARBOMER INTERPOLYMER TYPE A (ALLYL SUCROSE CROSSLINKED); TROLAMINE; SODIUM PHOSPHATE; SODIUM CHLORIDE; EDETIC ACID; EDETATE DISODIUM; PHENOXYETHANOL; CAPRYLYL GLYCOL

De-Aging Moisturizing Day Creme With Sunscreen SPF 20

ACTIVE INGREDIENT

Active Ingredients Purpose Octinoxate 7.5%.............................. Sunscreen Octisalate 3.0%................................ Sunscreen Oxybenzone 3.0%............................. Sunscreen Titanium Dioxide 0.4%.......................Sunscreen

PURPOSE

Uses Helps prevent sunburn Higher SPF gives more sunburn protection.

Uses

Helps prevent sunburn.
Higher SPF gives more sunburn protection.

Warnings For External use only

Do not use on irritated or broken skin.

Stop use and ask a physician if rash, irritation or sensitivity develops and lasts.

When using this product do not get into eyes, if contact occurs, rinse eyes thoroughly with water.

Keep out of reach of chidren.

In case of accidental ingestion, get medical help or contact a Poison Control Center right away.

DOSAGE AND ADMINISTRATION

Directions - Apply to clean skin for daily sun protection - Allow to absorb - Ask a doctor before use on children under 3 years of age.

Other Information Sun Alert: Limiting sun exposure, wearing protective clothing, and using sunscreen may reduce the risks of skin aging, skin cancer and other harmful effects of the sun.

INACTIVE INGREDIENT

Inactive Ingredients: Water, Propylene Glycol, Caprylic/Capric Triglyceride, Glyceryl Stearate, PEG-100 Stearate, Stearic Acid, C12-15 Alkyl Benzoate, Sodium Hyaluronate, Butylene Glycol, Ceramide 2, Human Oligcpeptide-9, Teprenonal, Lonicers Caprifolium (Honeysuckle) Flower Extract, Zizyphus Jujuba Fruit Extract, Glycymhiza Glabra (licorice) Root Extract, Retinyl Palmitate, Tocopheryl Acetate, Cetyl Alcohol Dimethicone, Alumina, Allantein, Panthenol, Sodium PCA, Lecithin, Acrylates/C10-30 Alkyl Acrylate Crosspolymer, Triethanolamine, Sodium Phosphate, Sodium Chloride, EDTA, Disodium EDTA, Phenoxyethanol, Caprylyl Glycol, Fragrance.

DESCRIPTION

De-Aging Moisturing Day Creme With Sunscreen SPF 20 This light and oil-free creme may be used as a base for makeup application. Promotes ultimate hydration for smoother, healthier-looking skin.

PACKAGE LABEL

ceLLuLaR laboratories net vol. 2 fl. oz./60 mL

PACKAGE LABEL

Manufactured for and exclusively distributed in the U.S. by: Market America, Inc. 1302 Pleasant Ridge Road Greensboro, NC 27409 Imported and exclusively distributed by: Market Hong Kong, Inc., in Hong Kong Unit 1615-1620, Level 16, Tower II Grend Century Place 193 Prince Edward Road West Mongkok, Kowloon, Hong Kong. Market America, Inc., in Canada 100 Wilkinson Road, Unit 5-6 Brampton, Ontario L6T 4Y9. Market Australia, Inc., in Australia Unit 2/36 Liverpool St. Ingleburn, NSW 2565

Drug Facts

PACKAGE LABEL

Drug Facts (continued)